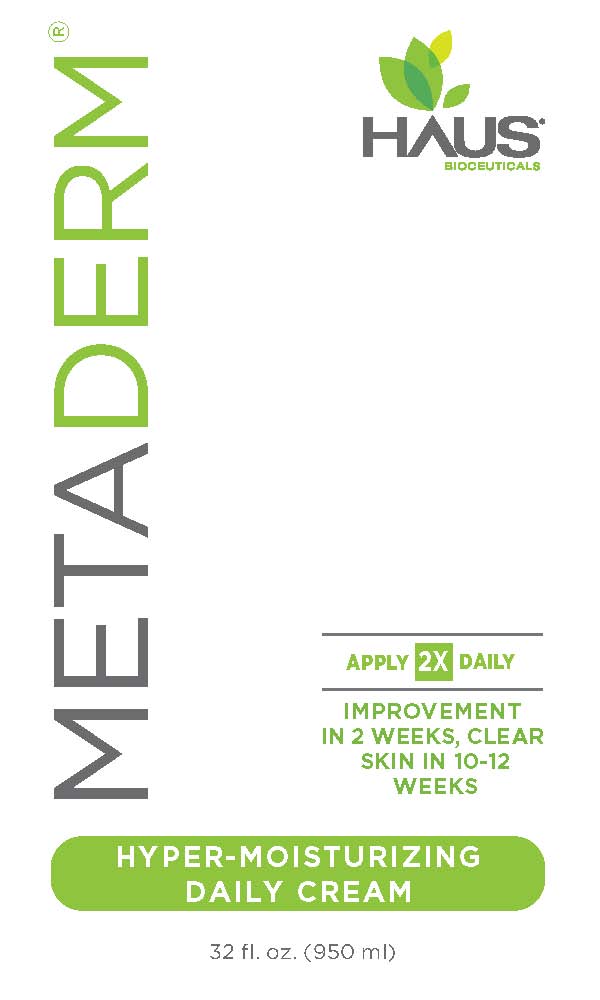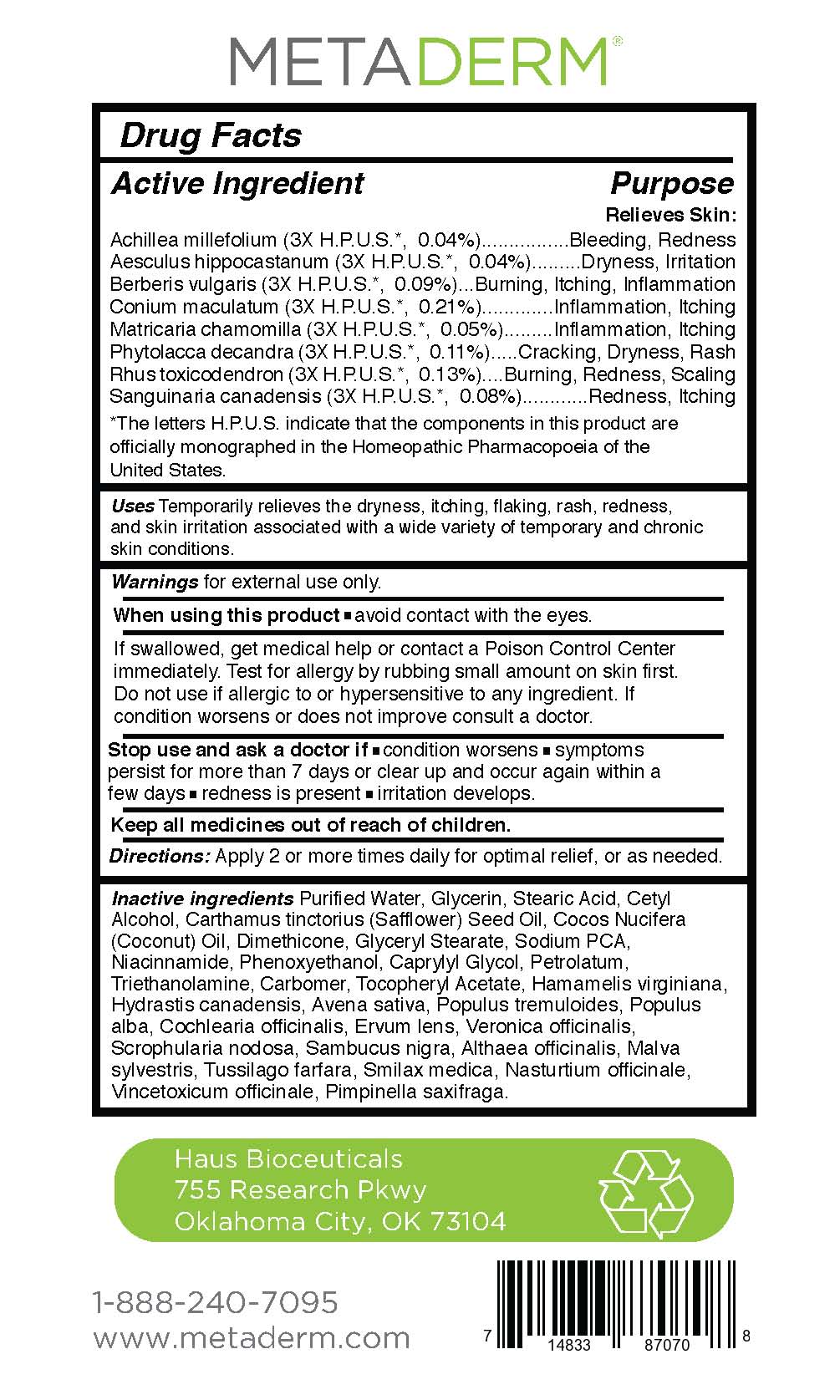 DRUG LABEL: Metaderm Hyper-Moisturizing Daily Cream
NDC: 58133-350 | Form: CREAM
Manufacturer: Cosmetic Specialty Labs, Inc.
Category: homeopathic | Type: HUMAN OTC DRUG LABEL
Date: 20180815

ACTIVE INGREDIENTS: MATRICARIA CHAMOMILLA FLOWERING TOP OIL 5 [hp_M]/1 mL; SANGUINARIA CANADENSIS ROOT 8 [hp_M]/1 mL; ACHILLEA MILLEFOLIUM 4 [hp_M]/1 mL; BERBERIS VULGARIS FRUIT 9 [hp_M]/1 mL; CONIUM MACULATUM FRUIT 21 [hp_M]/1 mL; RHUS SPP. WHOLE 13 [hp_M]/1 mL; PHYTOLACCA OCTANDRA LEAF 11 [hp_M]/1 mL; AESCULUS HIPPOCASTANUM SEED OIL 4 [hp_M]/1 mL
INACTIVE INGREDIENTS: CARTHAMUS TINCTORIUS (SAFFLOWER) OLEOSOMES; VERONICA OFFICINALIS LEAF; ALTHAEA OFFICINALIS LEAF; SCROPHULARIA NODOSA; WATER; ALPHA-TOCOPHEROL ACETATE; TRIETHANOLAMINE LAURYLAMINOPROPIONATE; CETYL ALCOHOL; HAMAMELIS VIRGINIANA ROOT BARK/STEM BARK; PHENOXYETHANOL; CAPRYLYL GLYCOL; CARBOMER 940; DIMETHICONE; HYDRASTIS CANADENSIS WHOLE; LENS CULINARIS FRUIT; SAMBUCUS NIGRA FLOWER OIL; MALVA SYLVESTRIS LEAF; TUSSILAGO FARFARA; STEARIC ACID; NIACINAMIDE; SODIUM PYRROLIDONE CARBOXYLATE; AVENA SATIVA LEAF; POPULUS TREMULOIDES LEAF; POPULUS ALBA LEAF; COCHLEARIA OFFICINALIS LEAF; SARSAPARILLA; NASTURTIUM OFFICINALE; VINCETOXICUM ATRATUM ROOT; PIMPINELLA SAXIFRAGA ROOT; GLYCERYL STEARATE SE; PETROLATUM; COCOS NUCIFERA WHOLE; GLYCERIN

Metaderm Hyper-Moisturizing Daily Cream

Active Ingredient

Achillea millefolium (3X H.P.U.S.*, 0.04%)
Aesculus hippocastanum (3X H.P.U.S.*, 0.04%)
Berberis vulgaris (3X H.P.U.S.*, 0.09%)
Conium maculatum (3X H.P.U.S.*, 0.21%)
Matricaria chamomilla (3X H.P.U.S.*, 0.05%)
Phytolacca decandra (3X H.P.U.S.*, 0.11%)
Rhus toxicodendron (3X H.P.U.S.*, 0.13%)
Sanguinaria canadensis (3X H.P.U.S.*, 0.08%)

Purpose

Relieves temporary and chronic skin conditions

*The letters H.P.U.S. indicate that the components in this product are officially monographed in the Homeopathic Pharmacopoeia of the United States.

Uses:

Temporarily relieves the dryness, itching, flaking, rash, redness,
and skin irritation associated with with a wide variety of temporary and chronic
skin conditions.

Warnings:

for external use only

When using this product:

- Avoid contact with eyes.
- If swallowed, get medical help or contact a Poison Control Center immediately.
- Test for allergy by rubbing small amount on skin first.
- Do not use if allergic to or hypersensitive to any ingredient.
- If condition worsens or does not improve consult a doctor.

Stop use and ask a doctor if:

- condition worsens
- symptoms persist for more than 7 days or clear up and occur again within a few days
- redness is present
- irritation develops

Keep all medicines out of reach of children.

Directions:

Apply 2 or more times daily for optimal relief, or as needed.

Other ingredients:

Purified Water, Glycerin, Stearic Acid, Cetyl
Alcohol, Carthamus tinctorius (Safflower) Seed Oil, Cocos Nucifera
(Coconut) Oil, Dimethicone, Glyceryl Stearate, Sodium PCA,
Niacinnamide, Phenoxyethanol, Caprylyl Glycol, Petrolatum,
Triethanolamine, Carbomer, Tocopheryl Acetate, Hamamelis virginiana,
Hydrastis canadensis, Avena sativa, Populus tremuloides, Populus
alba, Cochlearia officinalis, Ervum lens, Veronica officinalis,
Scrophularia nodosa, Sambucus nigra, Althaea officinalis, Malva
sylvestris, Tussilago farfara, Smilax medica, Nasturtium officinale,
Vincetoxicum officinale, Pimpinella saxifraga.